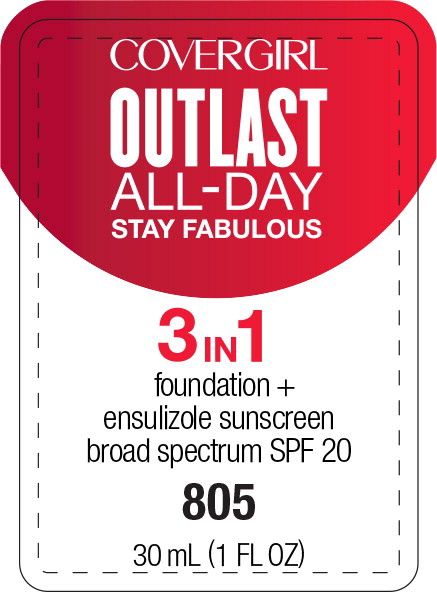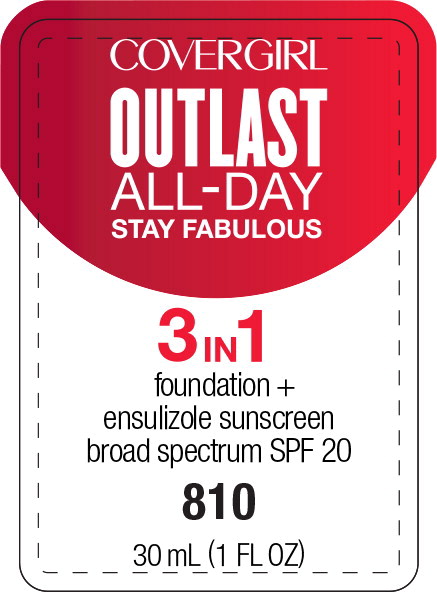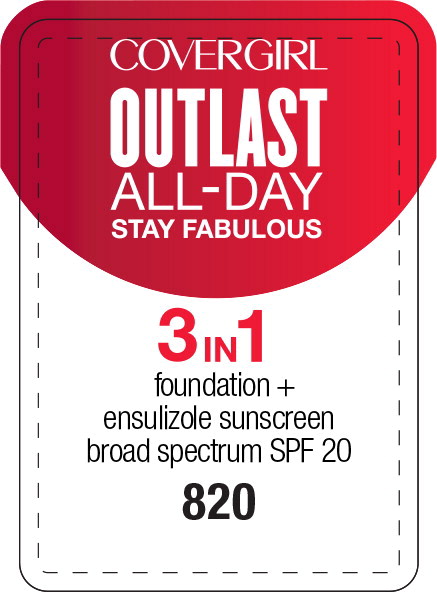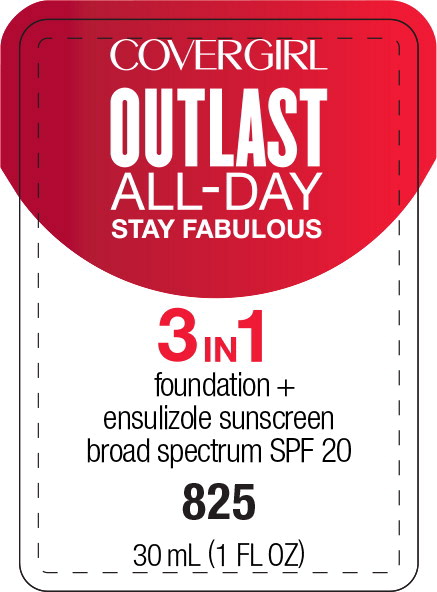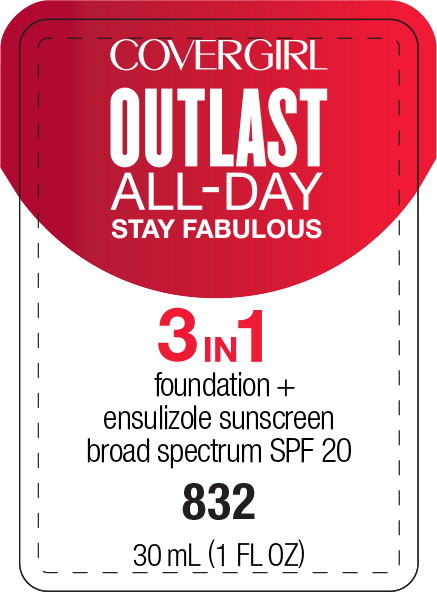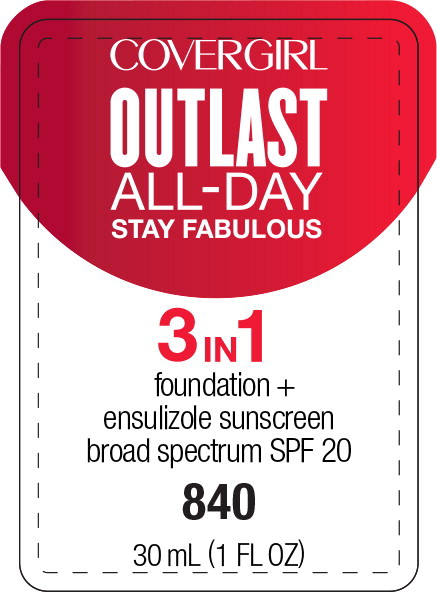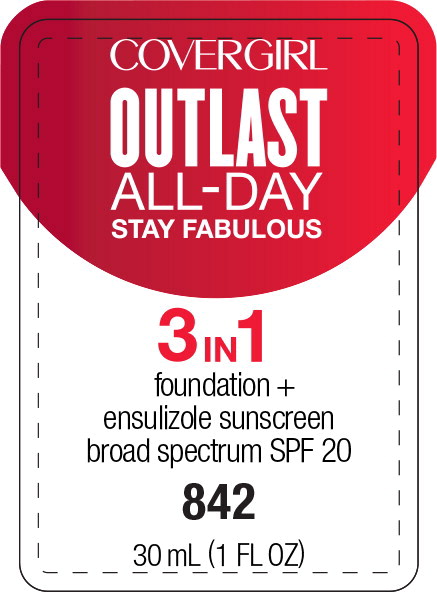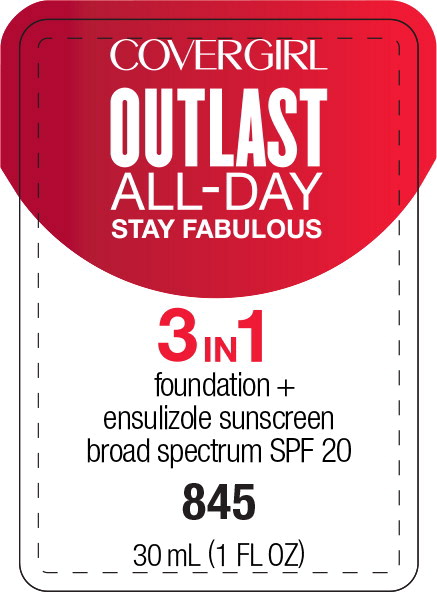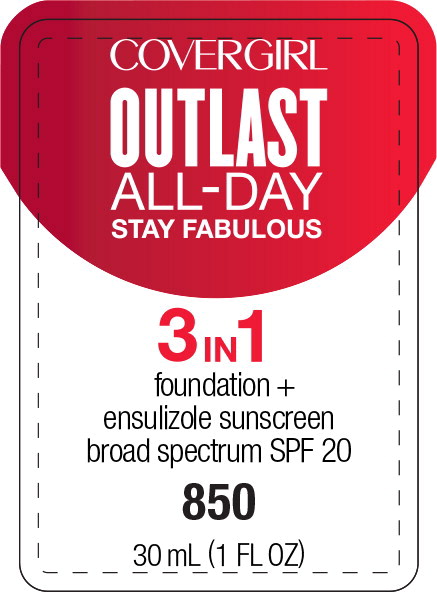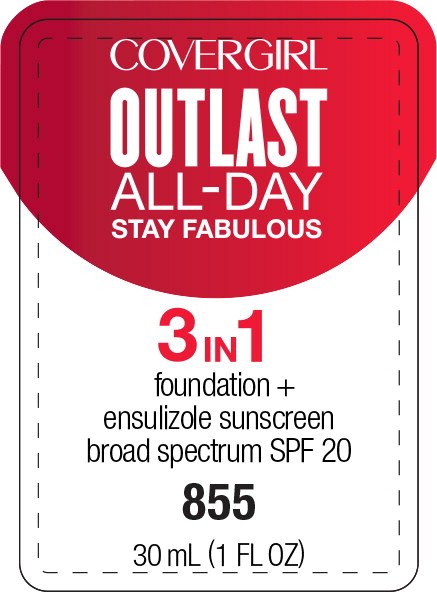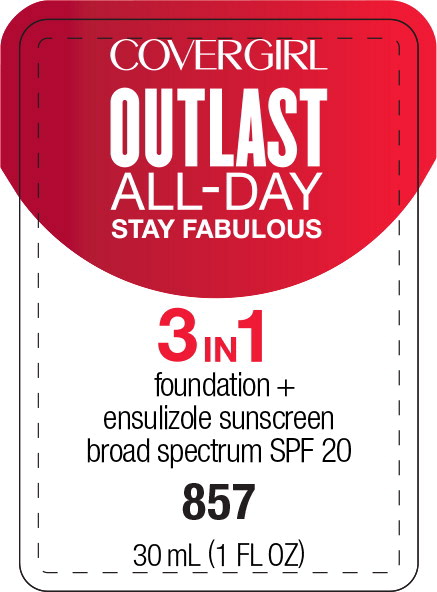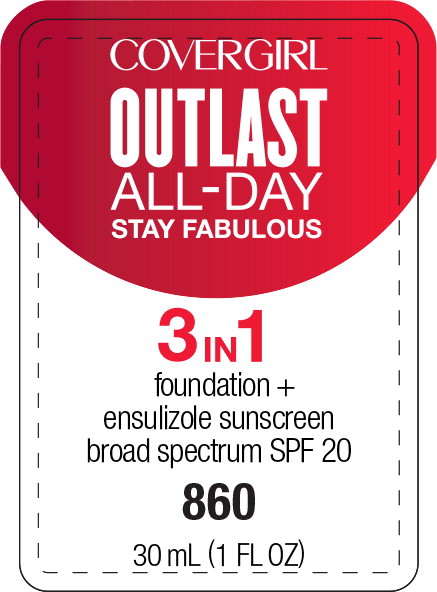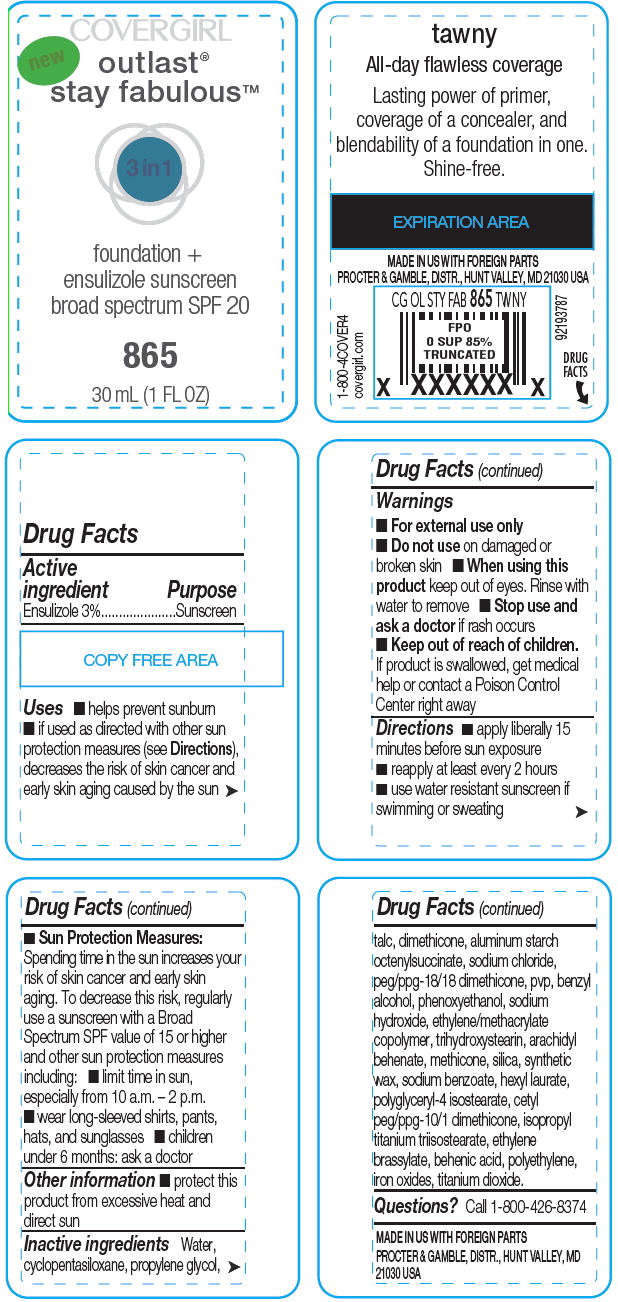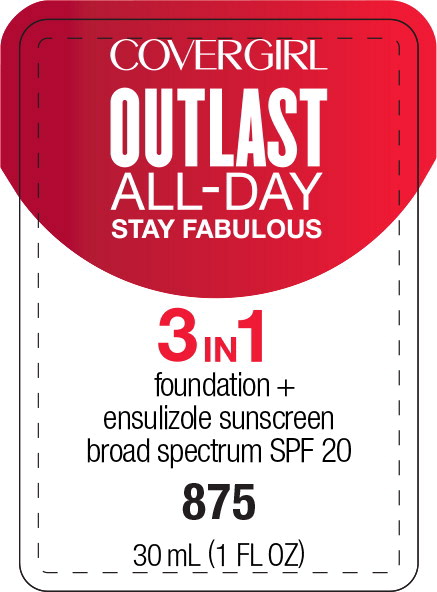 DRUG LABEL: Covergirl Outlast Stay Fabulous 3in1 Foundation 


NDC: 22700-127 | Form: LIQUID
Manufacturer: Noxell
Category: otc | Type: HUMAN OTC DRUG LABEL
Date: 20230128

ACTIVE INGREDIENTS: ENSULIZOLE 0.03 mg/1 mL
INACTIVE INGREDIENTS: WATER; CYCLOMETHICONE 5; PROPYLENE GLYCOL; TALC; DIMETHICONE; ALUMINUM STARCH OCTENYLSUCCINATE; SODIUM CHLORIDE; PEG/PPG-18/18 DIMETHICONE; BENZYL ALCOHOL; PHENOXYETHANOL; SODIUM HYDROXIDE; TRIHYDROXYSTEARIN; ARACHIDYL BEHENATE; SILICON DIOXIDE; SODIUM BENZOATE; HEXYL LAURATE; POLYGLYCERYL-4 ISOSTEARATE; ISOPROPYL TITANIUM TRIISOSTEARATE; ETHYLENE BRASSYLATE; BEHENIC ACID; HIGH DENSITY POLYETHYLENE; TITANIUM DIOXIDE

Covergirl Outlast® Stay Fabulous™ 3in1 Foundation
Broad spectrum SPF 20

Drug Facts

Active ingredient

Ensulizole 3%

Purpose

Sunscreen

Uses

- helps prevent sunburn
- if used as directed with other sun protection measures (see Directions), decreases the risk of skin cancer and early skin aging caused by the sun

Warnings

- For external use only

- Do not use on damaged or broken skin

- When using this product keep out of eyes. Rinse with water to remove

- Stop use and ask a doctor if rash occurs

- Keep out of reach of children. If product is swallowed, get medical help or contact a Poison Control Center right away

Directions

- apply liberally 15 minutes before sun exposure
- reapply at least every 2 hours
- use water resistant sunscreen if swimming or sweating
- Sun Protection Measures: Spending time in the sun increases your risk of skin cancer and early skin aging. To decrease this risk, regularly use a sunscreen with a Broad Spectrum SPF value of 15 or higher and other sun protection measures including:
  - limit time in sun, especially from 10 a.m. – 2 p.m.
  - wear long-sleeved shirts, pants, hats, and sunglasses
- children under 6 months: ask a doctor

Other information

- protect this product from excessive heat and direct sun

Inactive ingredients

Water, cyclopentasiloxane, propylene glycol, talc, dimethicone, aluminum starch octenylsuccinate, sodium chloride, peg/ppg-18/18 dimethicone, pvp, benzyl alcohol, phenoxyethanol, sodium hydroxide, ethylene/methacrylate copolymer, trihydroxystearin, arachidyl behenate, methicone, silica, synthetic wax, sodium benzoate, hexyl laurate, polyglyceryl-4 isostearate, cetyl peg/ppg-10/1 dimethicone, isopropyl titanium triisostearate, ethylene brassylate, behenic acid, polyethylene, iron oxides, titanium dioxide.

Questions?

Call 1-800-426-8374

PROCTER & GAMBLE, DISTR., HUNT VALLEY, MD 21030 USA

Principal Display Panel - Covergirl Outlast All-Day 3 in 1 805 Label

COVERGIRL

OUTLAST
ALL-DAY
STAY FABULOUS

3 in 1

foundation +
ensulizole sunscreen
broad spectrum SPF 20

805

30 mL (1 FL OZ)

Principal Display Panel - Covergirl Outlast All-Day 3 in 1 810 Label

COVERGIRL

OUTLAST
ALL-DAY
STAY FABULOUS

3 in 1

foundation +
ensulizole sunscreen
broad spectrum SPF 20

810

30 mL (1 FL OZ)

Principal Display Panel - Covergirl Outlast All-Day 3 in 1 820 Label

COVERGIRL

OUTLAST
ALL-DAY
STAY FABULOUS

3 in 1

foundation +
ensulizole sunscreen
broad spectrum SPF 20

820

30 mL (1 FL OZ)

Principal Display Panel - Covergirl Outlast All-Day 3 in 1 825 Label

COVERGIRL

OUTLAST
ALL-DAY
STAY FABULOUS

3 in 1

foundation +
ensulizole sunscreen
broad spectrum SPF 20

825

30 mL (1 FL OZ)

Principal Display Panel - Covergirl Outlast All-Day 3 in 1 832 Label

COVERGIRL

OUTLAST
ALL-DAY
STAY FABULOUS

3 in 1

foundation +
ensulizole sunscreen
broad spectrum SPF 20

832

30 mL (1 FL OZ)

Principal Display Panel - Covergirl Outlast All-Day 3 in 1 840 Label

COVERGIRL

OUTLAST
ALL-DAY
STAY FABULOUS

3 in 1

foundation +
ensulizole sunscreen
broad spectrum SPF 20

840

30 mL (1 FL OZ)

Principal Display Panel - Covergirl Outlast All-Day 3 in 1 842 Label

COVERGIRL

OUTLAST
ALL-DAY
STAY FABULOUS

3 in 1

foundation +
ensulizole sunscreen
broad spectrum SPF 20

842

30 mL (1 FL OZ)

Principal Display Panel - Covergirl Outlast All-Day 3 in 1 845 Label

COVERGIRL

OUTLAST
ALL-DAY
STAY FABULOUS

3 in 1

foundation +
ensulizole sunscreen
broad spectrum SPF 20

845

30 mL (1 FL OZ)

Principal Display Panel - Covergirl Outlast All-Day 3 in 1 850 Label

COVERGIRL

OUTLAST
ALL-DAY
STAY FABULOUS

3 in 1

foundation +
ensulizole sunscreen
broad spectrum SPF 20

850

30 mL (1 FL OZ)

Principal Display Panel - Covergirl Outlast All-Day 3 in 1 855 Label

COVERGIRL

OUTLAST
ALL-DAY
STAY FABULOUS

3 in 1

foundation +
ensulizole sunscreen
broad spectrum SPF 20

855

30 mL (1 FL OZ)

Principal Display Panel - Covergirl Outlast All-Day 3 in 1 857 Label

COVERGIRL

OUTLAST
ALL-DAY
STAY FABULOUS

3 in 1

foundation +
ensulizole sunscreen
broad spectrum SPF 20

857

30 mL (1 FL OZ)

Principal Display Panel - Covergirl Outlast All-Day 3 in 1 860 Label

COVERGIRL

OUTLAST
ALL-DAY
STAY FABULOUS

3 in 1

foundation +
ensulizole sunscreen
broad spectrum SPF 20

860

30 mL (1 FL OZ)

PRINCIPAL DISPLAY PANEL - 865 - 30 mL Bottle Label

COVERGIRL

new

outlast®
stay fabulous™

3 in 1

foundation +
ensulizole sunscreen
broad spectrum SPF 20

865

30 mL (1 FL OZ)

Principal Display Panel - Covergirl Outlast All-Day 3 in 1 875 Label

COVERGIRL

OUTLAST
ALL-DAY
STAY FABULOUS

3 in 1

foundation +
ensulizole sunscreen
broad spectrum SPF 20

875

30 mL (1 FL OZ)